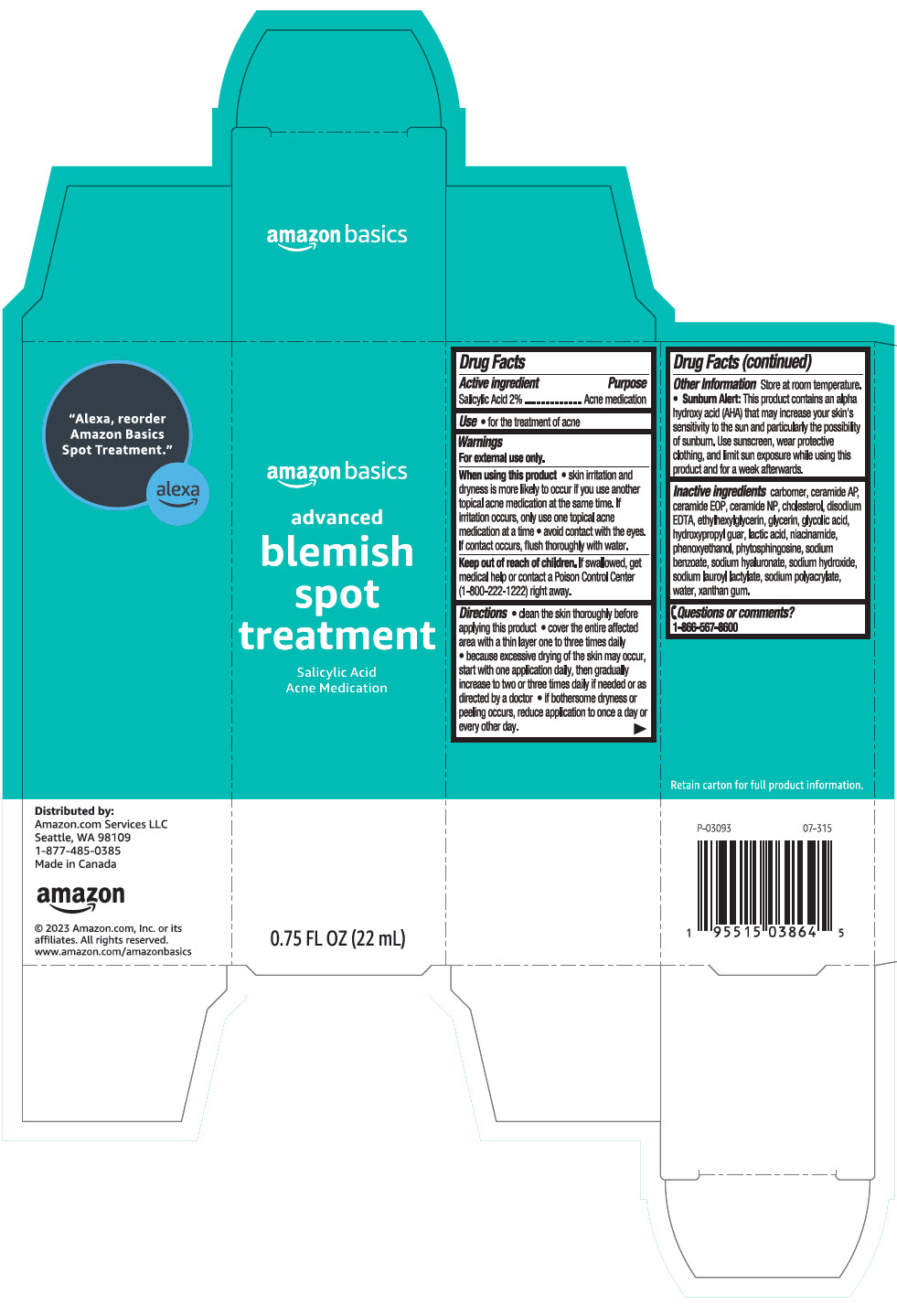 DRUG LABEL: amazon basics advanced blemish spot treatment
NDC: 72288-386 | Form: LOTION
Manufacturer: AMAZON.COM SERVICES LLC
Category: otc | Type: HUMAN OTC DRUG LABEL
Date: 20241114

ACTIVE INGREDIENTS: SALICYLIC ACID 20 mg/1 mL
INACTIVE INGREDIENTS: CARBOMER HOMOPOLYMER, UNSPECIFIED TYPE; Ceramide AP; CERAMIDE 1; Ceramide NP; Cholesterol; EDETATE DISODIUM; Ethylhexylglycerin; Glycerin; Glycolic Acid; GUARAPROLOSE (3500 MPA.S AT 1%); LACTIC ACID, UNSPECIFIED FORM; Niacinamide; Phenoxyethanol; Phytosphingosine; Sodium Benzoate; HYALURONATE SODIUM; Sodium Hydroxide; Sodium Lauroyl Lactylate; SODIUM POLYACRYLATE (2500000 MW); Water; Xanthan Gum

amazon basics advanced blemish spot treatment
Acne medication

Drug Facts

Active ingredient

Salicylic Acid 2%

Purpose

Acne medication

Use

- for the treatment of acne

Warnings

For external use only.

When using this product

- skin irritation and dryness is more likely to occur if you use another topical acne medication at the same time. If irritation occurs, only use one topical acne medication at a time.
- avoid contact with the eyes. If contact occurs, flus thoroughly with water.

Keep out of reach of children. If swallowed, get medical help or contact a Poison Control Center (1-800-222-1222) right away.

Directions

- clean the skin thoroughly before applying this product

- cover the entire affected area with a thin layer one to three times daily
- because excessive drying of the skin may occur, start with one application daily, then gradually increase to two or three times daily if needed or as directed by a doctor
- if bothersome dryness or peeling occurs, reduce application to once a day or every other day

Other Information

store at room temperature.

- Sunburn Alert: This product contains an alpha hydroxy acid (AHA) that may increase your skin's sensitivity to the sun and particularly the possibility of sunburn. Use sunscreen, wear protective clothing, and limit sun exposure while using this product and for a week afterwards.

Inactive ingredients

carbomer, ceramide AP, ceramide EOP, ceramide NP, cholesterol, disodium EDTA, ethylhexylglycerin, glycerin, glycolic acid, hydroxypropyl guar, lactic acid, niacinamide, phenoxyethanol, phytosphingosine, sodium benzoate, sodium hyaluronate, sodium hydroxide, sodium lauroyl lactylate, sodium polyacrylate, water, xanthan gum.

Questions or comments?

1-866-567-8600

Distributed by:
Amazon.com Services LLC
Seattle, WA 98109

PRINCIPAL DISPLAY PANEL - 22 mL Tube Carton

amazon basics

advanced
blemish
spot
treatment

Salicylic Acid
Acne Medication

0.75 FL OZ (22 mL)